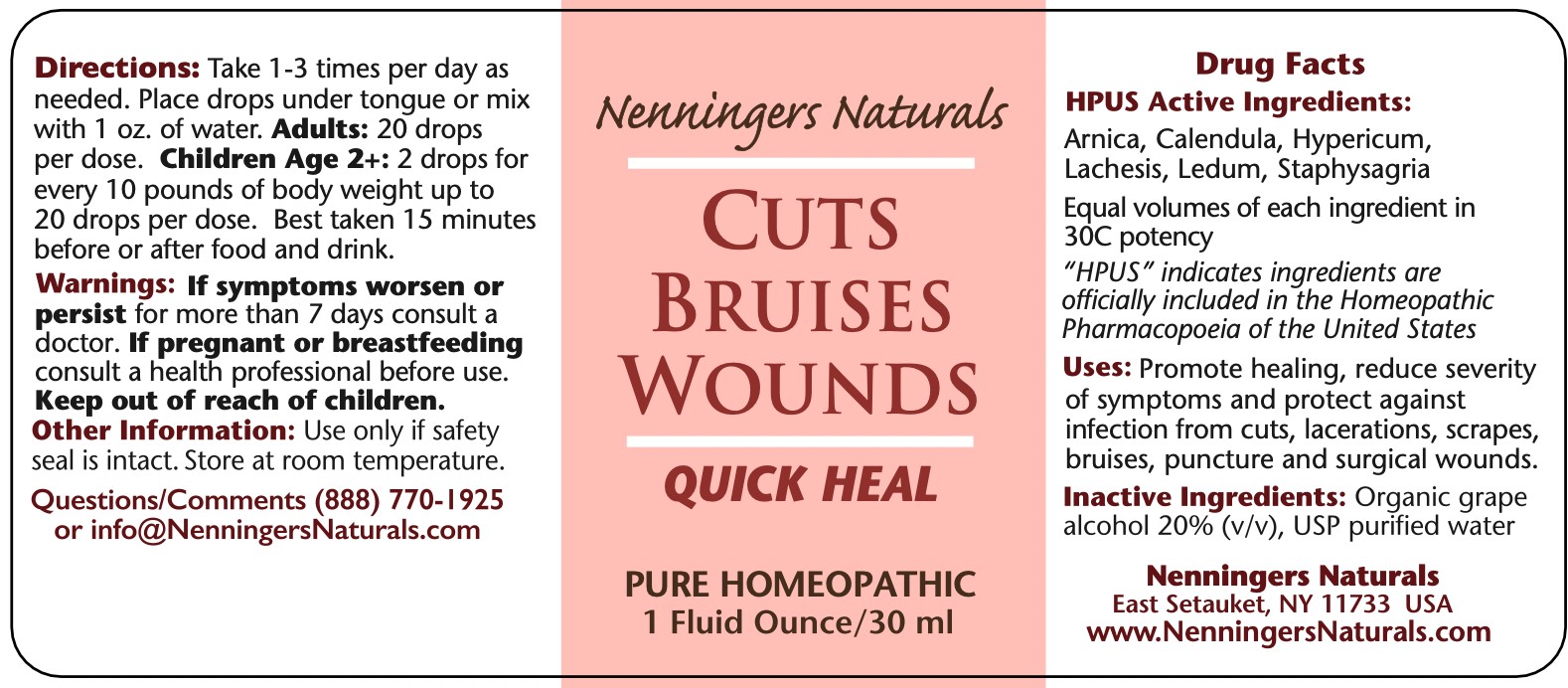 DRUG LABEL: Nenningers Naturals
NDC: 42731-076 | Form: LIQUID
Manufacturer: Nenningers Naturals, LLC
Category: homeopathic | Type: HUMAN OTC DRUG LABEL
Date: 20251225

ACTIVE INGREDIENTS: ARNICA MONTANA 30 [hp_C]/30 mL; CALENDULA OFFICINALIS FLOWERING TOP 30 [hp_C]/30 mL; ST. JOHN'S WORT 30 [hp_C]/30 mL; LACHESIS MUTA VENOM 30 [hp_C]/30 mL; DELPHINIUM STAPHISAGRIA SEED 30 [hp_C]/30 mL; LEDUM PALUSTRE TWIG 30 [hp_C]/30 mL
INACTIVE INGREDIENTS: ALCOHOL; WATER

Cuts Bruises Wounds

ACTIVE INGREDIENT

Active Ingredients: Arnica, Calendula, Hypericum, Lachesis, Ledum, Staphysagria, All HPUS.

Purpose: Homeopathic medicine for symptom relief from cuts, bruises and wounds.

PURPOSE

Homeopathic medicine for symptom relief from cuts, bruises and wounds.

INACTIVE INGREDIENT

alcohol, USP purified Water

Uses:

Promotes healing, reduce the severity of symptoms, and protect against infection from cuts, lacerations, scrapes, bruises, puncture, and surgical wounds.

Warnings:

If symptoms worsen or persist for more than 3 days, consult a physician.

If pregnant or breastfeeding, consult a physician before use.

Keep out of reach of children.

Directions:

Take 1 to 3 times per day as needed. Place drops under the tongue or mix with 1 oz. of water. Adults: 20 drops
per dose. Children Age 2+: 2 drops for every 10 pounds of body weight up to
20 drops per dose. Best taken 15 minutes before or after the food and drink.

Other information:

Use only if safety seal is intact. Store at room temperature, away from direct sublight.

Keep out of reach of children

Package: 30mL. NDC: 42731-076-01